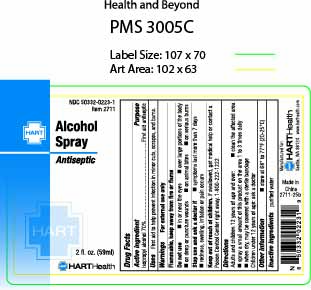 DRUG LABEL: Alcohol
NDC: 50332-0223 | Form: SPRAY
Manufacturer: NorMed
Category: otc | Type: HUMAN OTC DRUG LABEL
Date: 20250815

ACTIVE INGREDIENTS: ISOPROPYL ALCOHOL 70 mL/100 mL
INACTIVE INGREDIENTS: WATER

Alcohol Spray

Active Ingredient:

Isopropyl Alcohol 70%

Purpose:

First aid antiseptic

Uses:

First aid to help prevent infection in minor cuts, scrapes, and burns

Warnings

For external use only

Flammable, keep away from fire or flames

Do not use

- in or near the eyes
- over large portions of the body
- on deep or puncture wounds
- on animal bites
- on serious burns

Stop use and ask a doctor if

- symptoms last more than 7 days
- redness, swelling, irritation or pain occurs

Keep out of reach of children.

If swallowed, get medical help or contact a Poison Control Center right away. 1-800-222-1222

Directions:

Adults and children 12 years of age and over:

- clean the affected area
- spray a small amount of this product on the area 1 to 3 times daly
- when dry. may be covered with a sterile bandage

Children under 12 years of age: ask a doctor

OTHER SAFETY INFORMATION

- store at 68° to 77°F (20-25°C)

Inactive ingredient

Purified Water